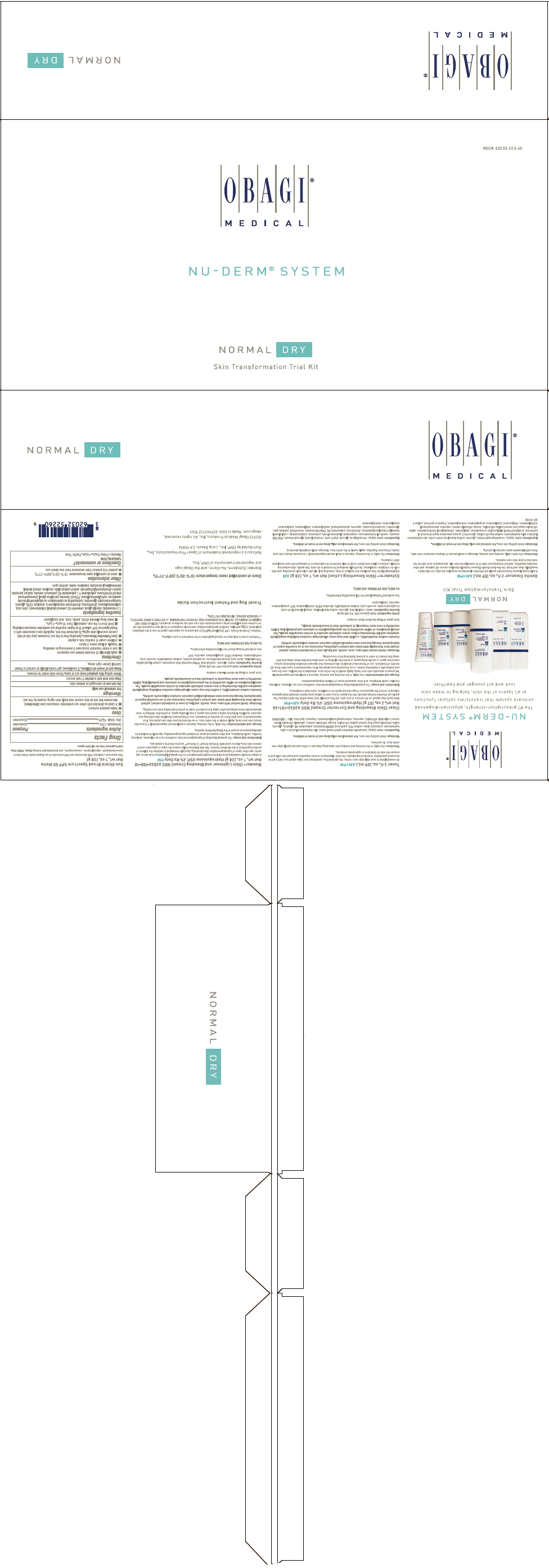 DRUG LABEL: nu-derm system normal-dry
NDC: 62032-522 | Form: KIT | Route: TOPICAL
Manufacturer: Obagi Cosmeceuticals LLC
Category: prescription | Type: HUMAN PRESCRIPTION DRUG LABEL
Date: 20191114

ACTIVE INGREDIENTS: HYDROQUINONE 40 mg/1 g; HYDROQUINONE 40 mg/1 g; OCTINOXATE 75 mg/1 g; ZINC OXIDE 105 mg/1 g
INACTIVE INGREDIENTS: EDETATE DISODIUM; PPG-2 MYRISTYL ETHER PROPIONATE; TROLAMINE SALICYLATE; SODIUM LAURYL SULFATE; CETYL ALCOHOL; GLYCERIN; LACTIC ACID, UNSPECIFIED FORM; .ALPHA.-TOCOPHEROL ACETATE; ASCORBIC ACID; SODIUM METABISULFITE; WATER; METHYLPARABEN; PROPYLPARABEN; BUTYLATED HYDROXYTOLUENE; PHENYL TRIMETHICONE; EDETATE DISODIUM; BUTYLPARABEN; STEARYL ALCOHOL; SODIUM LAURYL SULFATE; CETYL ALCOHOL; GLYCERIN; LACTIC ACID, UNSPECIFIED FORM; .ALPHA.-TOCOPHEROL ACETATE; ASCORBIC ACID; SODIUM METABISULFITE; WATER; METHYLPARABEN; PROPYLPARABEN; BUTYLATED HYDROXYTOLUENE; WATER; GLYCERIN; PHENOXYETHANOL; XANTHAN GUM; CHLORPHENESIN; CYCLOMETHICONE 5; PENTYLENE GLYCOL; PHENYL TRIMETHICONE; HYDROXYETHYL ACRYLATE/SODIUM ACRYLOYLDIMETHYL TAURATE COPOLYMER (100000 MPA.S AT 1.5%); SQUALANE; POLYSORBATE 60; PEG-40 STEARATE; DIMETHICONE; STEARYL ALCOHOL; CETOSTEARYL ALCOHOL; SODIUM DIHYDROXYCETYL PHOSPHATE; HYDROGENATED PALM GLYCERIDES; POLYOXYL 20 CETOSTEARYL ETHER; 1,2-HEXANEDIOL; CAPRYLYL GLYCOL; TROPOLONE; CITRIC ACID MONOHYDRATE; EDETATE DISODIUM; POTASSIUM SORBATE; SODIUM BENZOATE; METHYLISOTHIAZOLINONE; TETRAHEXYLDECYL ASCORBATE; SODIUM POLYACRYLATE (2500000 MW)

NU-DERM® SYSTEM
NORMAL DRY
Skin Transformation Trial Kit

Clear (Skin Bleaching and Corrector Cream) NDC 62032-101-36 Net wt. 2 oz. (57 g) Hydroquinone USP, 4% Rx Only AM+PM

Dark spots may appear on the surface of your skin, but they actually start deep within the skin's layers. This gentle yet effective formula absorbs into the layers of your skin to deliver prescription-strength hydroquinone, helping to correct the appearance of age and sun spots for a healthier, more even complexion.

Indications and usage

The gradual bleaching of hyperpigmented skin conditions such as chloasma, melasma, freckles, senile lentigines, and other unwanted areas of melanin hyperpigmentation.

Dosage and administration

Use daily, in the morning and evening. Squeeze a small amount (approximately 1-2 pea-size amounts) onto your hand. Apply evenly to the entire face, extending to the hairline, over the ears, and ending with a feathering motion, or as directed by your physician. If no improvement is seen after three (3) months of treatment, use of this product should be discontinued. Sun exposure should be limited by using a sunscreen agent, a sun blocking agent, or protective clothing to cover bleached skin when using and after using this product in order to prevent darkening from reoccurring.

Warnings

Avoid contact with eyes, nose, mouth, and lips. In case of accidental contact, patient should rinse thoroughly with water and contact a physician. Sunscreen use is an essential aspect of hydroquinone therapy because even minimal sunlight exposure sustains melanocytic activity.

Contains sodium metabisulfite, a sulfite that may cause allergic-type reactions including anaphylactic symptoms and life-threatening or less severe asthmatic episodes in certain susceptible people. The overall prevalence of sulfite sensitivity in the general population is unknown and probably low. Sulfite sensitivity is seen more frequently in asthmatic than in nonasthmatic people.

DESCRIPTION

Each gram of Obagi Nu-Derm Clear contains:

Active ingredient

Hydroquinone USP, 4% (40 mg/g)

Inactive ingredients

water, cetyl alcohol, glycerin, sodium lauryl sulfate, stearyl alcohol, lactic acid, tocopheryl acetate, ascorbic acid, sodium metabisulfite, disodium EDTA, methylparaben, BHT, propylparaben, saponins, butylparaben

See enclosed Package Insert for full prescribing information.

Rx ONLY. FOR EXTERNAL USE ONLY.

Blender® (Skin Lightener and Blending Cream) NDC 62032-100-10 Net wt. 1 oz. (28 g) Hydroquinone USP, 4% Rx Only PM

A unique formula containing prescription-strength hydroquinone for the gradual lightening of sun spots, age spots, and other types of hyperpigmentation (discoloration). Specially formulated to optimize the delivery of product ingredients in the Nu-Derm System, this skin lightener helps reduce the signs of aging and correct uneven skin tone. May be used with Tretinoin Cream [Tretinoin cream is indicated for topical application in the treatment of acne vulgaris.] or Refissa® [Refissa [Tretinoin Cream, USP (Emollient) 0.05%] is indicated as an adjunctive agent for use in the mitigation (palliation) of fine wrinkles, mottled hyperpigmentation, and tactile roughness of facial skin in patients who do not achieve such palliation using comprehensive skin care and sun avoidance programs. REFISSA DOES NOT ELIMINATE WRINKLES, REPAIR SUN-DAMAGED SKIN, REVERSE PHOTOAGING, or RESTORE A MORE YOUTHFUL or YOUNGER DERMAL HISTOLOGIC PATTERN.] as prescribed by a physician.

Indications and usage

The gradual bleaching of hyperpigmented skin conditions such as chloasma, melasma, freckles, senile lentigines, and other unwanted areas of melanin hyperpigmentation. Specially formulated for blending purposes as part of the Obagi Nu-Derm System.

Dosage and administration

Use daily, in the evening. Squeeze a small amount (approximately 1-2 pea-size drops) onto your hand. Apply evenly to the entire face, or as directed by your skin care physician. If no improvement is seen after three (3) months of treatment, use of this product should be discontinued. Sun exposure should be limited by using a sunscreen agent, a sun blocking agent, or protective clothing to cover bleached skin when using and after using this product in order to prevent darkening from reoccurring.

Warnings

Avoid contact with eyes, nose, mouth, and lips. In case of accidental contact, patient should rinse thoroughly with water and contact a physician. Sunscreen use is an essential aspect of hydroquinone therapy because even minimal sunlight exposure sustains melanocytic activity.

Contains sodium metabisulfite, a sulfite that may cause allergic-type reactions including anaphylactic symptoms and life-threatening or less severe asthmatic episodes in certain susceptible people. The overall prevalence of sulfite sensitivity in the general population is unknown and probably low. Sulfite sensitivity is seen more frequently in asthmatic than in nonasthmatic people.

DESCRIPTION

Each gram of Obagi Nu-Derm Blender contains:

Active ingredient

Hydroquinone USP, 4% (40 mg/g)

Inactive ingredients

water, glycerin, cetyl alcohol, PPG-2 myristyl ether propionate, sodium lauryl sulfate, TEA-salicylate, lactic acid, phenyl trimethicone, tocopheryl acetate, sodium metabisulfite, ascorbic acid, methylparaben, disodium EDTA, propylparaben, saponins, BHT

See enclosed Package Insert for full prescribing information.

Rx ONLY. FOR EXTERNAL USE ONLY.

Travel Bag and Patient Instruction Guide

STORAGE AND HANDLING

Store at controlled room temperature 15°C–25°C (59°F–77°F).

Blender, Exfoderm, Nu-Derm, and the Obagi logo are registered trademarks of OMP, Inc.

Refissa is a registered trademark of Spear Pharmaceuticals, Inc.
Distributed by OMP, Inc., Long Beach, CA 90806

©2012 Obagi Medical Products, Inc. All rights reserved.
obagi.com Made in USA 40706311Z 7063

Sun Shield Broad Spectrum SPF 50 Matte Net wt. 1 oz. (28 g)

This sunscreen combines UVB absorption and UVA protection in an elegant matte finish that is non-comedogenic, hypoallergenic, non-acnegenic, and dermatologist tested. Sheer, PABA free,

Drug Facts

Active ingredients

Octinoxate 7.5%
Zinc Oxide 10.5%

Purpose

Sunscreen

Uses

- helps prevent sunburn
- if used as directed with other sun protection measures (see Directions), decreases the risk of skin cancer and early skin aging caused by the sun

Warnings

For external use only

Do not use on damaged or broken skin

Stop use and ask a doctor if rash occurs

When using this product keep out of eyes. Rinse with water to remove.

Keep out of reach of children. If swallowed, get medical help or contact a Poison Control Center right away.

Directions

- apply liberally 15 minutes before sun exposure
- use a water resistant sunscreen if swimming or sweating
- reapply at least every 2 hours
- children under 6 months: Ask a doctor
- Sun Protection Measures. Spending time in the sun increases your risk of skin cancer and early skin aging. To decrease this risk, regularly use a sunscreen with a Broad Spectrum SPF value of 15 or higher and other sun protection measures including:
  - limit time in the sun, especially from 10 a.m.–2 p.m.
  - wear long-sleeved shirts, pants, hats, and sunglasses

Inactive ingredients

1,2 hexanediol, caprylyl glycol, ceteareth-20, cetearyl alcohol, chlorphenesin, citric acid, cyclopentasiloxane, dimethicone, dimethicone crosspolymer-3, disodium EDTA, glycerin, hydrogenated palm glycerides, hydroxyethyl acrylate/sodium acryloyldimethyl taurate copolymer, methylisothiazolinone, PEG-40 stearate, pentylene glycol, phenoxyethanol, phenyl trimethicone, polysilicone-11, polysorbate 60, potassium sorbate, sodium benzoate, sodium dihydroxycetyl phosphate, sodium polyacrylate, squalane, stearyl alcohol, tetrahexyldecyl ascorbate, tropolone, water, xanthan gum

Other information

- store at controlled room temperature: 15°C–25°C (59°F–77°F)
- protect this product from excessive heat and direct sun

Questions or comments?

1.800.636.7546
Monday–Friday 9 a.m.–4 p.m. Pacific Time

PRINCIPAL DISPLAY PANEL - Kit Carton

NDC# 62032-522-60

OBAGI®
MEDICAL

NU-DERM® SYSTEM

NORMAL DRY

Skin Transformation Trial Kit